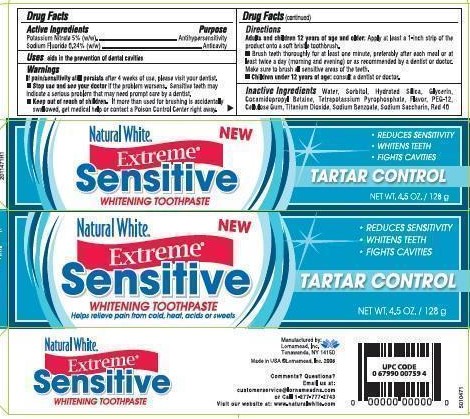 DRUG LABEL: Lornamead
NDC: 62721-0471 | Form: PASTE, DENTIFRICE
Manufacturer: Lornamead
Category: otc | Type: HUMAN OTC DRUG LABEL
Date: 20181229

ACTIVE INGREDIENTS: SODIUM FLUORIDE 0.24 g/100 g; POTASSIUM NITRATE 5 g/100 g
INACTIVE INGREDIENTS: SORBITOL; WATER; SACCHARIN SODIUM; SODIUM BENZOATE; POLYETHYLENE GLYCOL 600; SODIUM TRIPOLYPHOSPHATE; TITANIUM DIOXIDE; GLYCERIN; FD&C RED NO. 40; HYDRATED SILICA; COCAMIDOPROPYL BETAINE; CARBOXYMETHYLCELLULOSE SODIUM, UNSPECIFIED FORM

Natural White Extreme Sensitive Toothpaste

Drug Facts

Active ingredient

Potassium Nitrate 5% (w/w)

Sodium Fluoride 0.24% (w/w)

Purpose

Antihypersenstivity

Anticavity

Use

aids in the prevention of dental cavities

Warnings

If pain/sensitivity still persists after 4 weeks of use, please visit your dentist.

- Stop use and ask a dentist if the sensitivity problem worsens. Sensitive teeth may indicate a serious problem that may need prompt care.

- Keep out of reach of children. If more than used for brushing is accidentally swallowed, get medical help or contact a Poison Control Center right away.

Directions

Adults and children 12 years of age and older: Apply at least a 1-inch strip of the product onto a soft bristle toothbrush.

- Brush teeth thoroughly for at least one minute, twice a day (morning and evening) or as recommended by a dentist. Make sure to brush all sensitive areas of the teeth.
- Children under 12 years of age: consult a dentist or doctor.

INACTIVE INGREDIENT

Inactive ingredients Water, Sorbiotol, Hydrated Silica, Glycerin, Cocamidopropyl Betaine, PEG-12, Titanium Dioxide, Cellulose Gum, Flavor, Sodium Benzoate, Sodium Saccharin, Red 40

STORAGE AND HANDLING

Store in a cool dry place. Keep tube capped when not in use.

Manufactured by:

Lornamead, Inc.

Tonawanda, NY 14150

Made in USA

Comments? Questions?

Email us at: customerservice@lornamead.com

or call 1-877-777-2743

PACKAGE LABEL

Natural White

Extreme Sensitive

WHITENING TOOTHPASTE

TARTAR CONTROL

REDUCES SENSITIVITY

FIGHTS CAVITIES

NET WT. 4.5 OZ / 128 g